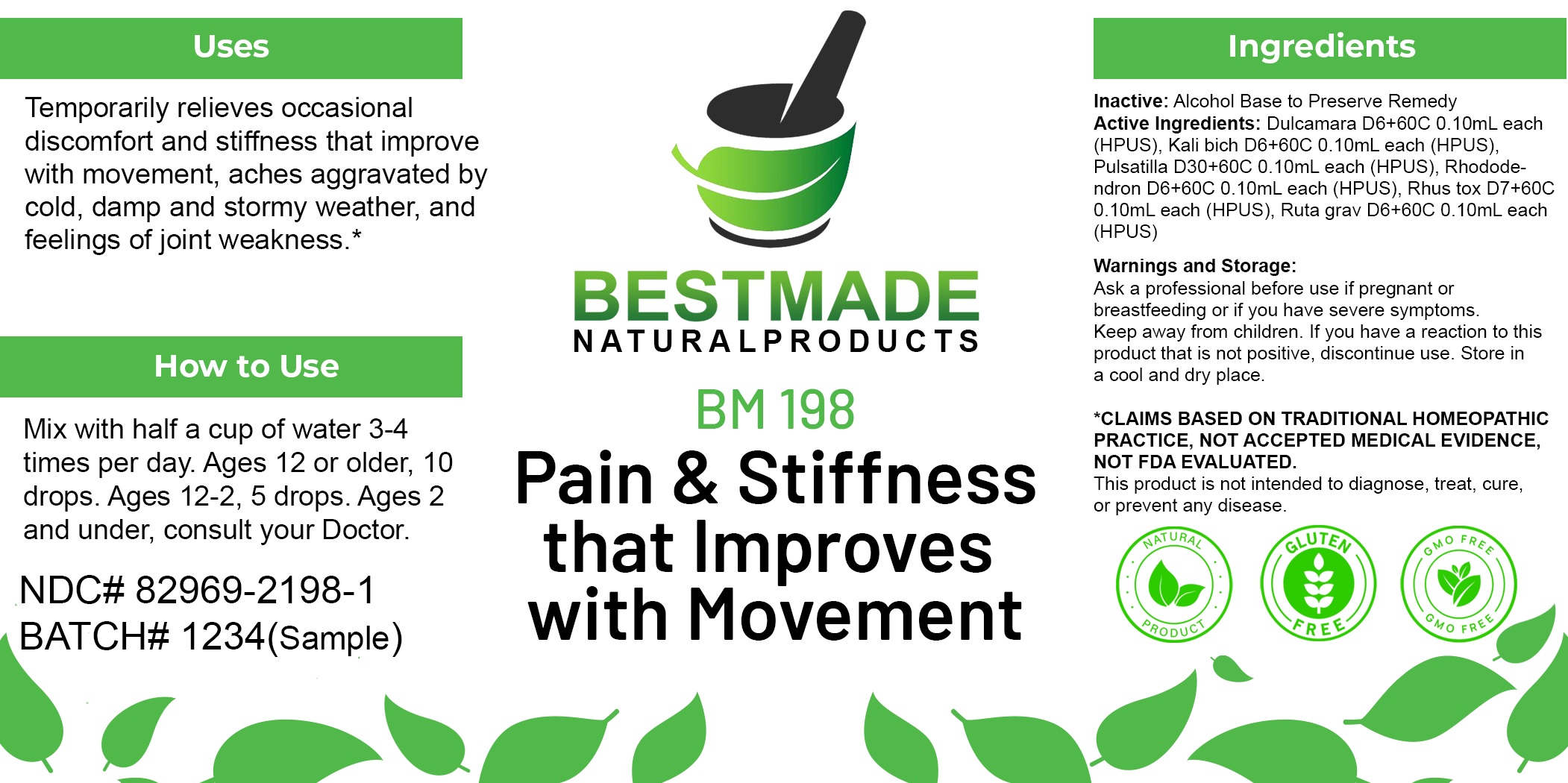 DRUG LABEL: Bestmade Natural Products BM198
NDC: 82969-2198 | Form: LIQUID
Manufacturer: Bestmade Natural Products
Category: homeopathic | Type: HUMAN OTC DRUG LABEL
Date: 20250225

ACTIVE INGREDIENTS: RUTA GRAVEOLENS FLOWERING TOP 30 [hp_C]/30 [hp_C]; SOLANUM DULCAMARA FLOWER 30 [hp_C]/30 [hp_C]; POTASSIUM DICHROMATE 30 [hp_C]/30 [hp_C]; TOXICODENDRON PUBESCENS LEAF 30 [hp_C]/30 [hp_C]; RHODODENDRON CAUCASICUM WHOLE 30 [hp_C]/30 [hp_C]; PULSATILLA PRATENSIS 30 [hp_C]/30 [hp_C]
INACTIVE INGREDIENTS: ALCOHOL 30 [hp_C]/30 [hp_C]

BM198

DOSAGE AND ADMINISTRATION

How to Use

Mix with half a cup of water 3-4 times per day. Ages 12 or older, 10 drops. Ages 12-2, 5 drops. Ages 2 and under, consult your Doctor.

Inactive:

Alcohol Base to Preserve Product

ACTIVE INGREDIENTS

Dulcamara D6+60C 0.10mL each (HPUS), Kali bich D6+60C 0.10mL each (HPUS), Pulsatilla D30+60C 0.10mL each (HPUS), Rhododendron D6+60C 0.10mL each (HPUS), Rhus tox D7+60C 0.10mL each (HPUS), Ruta grav D6+60C 0.10mL each (HPUS)

KEEP OUT OF REACH OF CHILDREN

Warnings and Storage:

Ask a professional before use if pregnant or breastfeeding or if you have severe symptoms.

Keep away from children. If you have a reaction to this product that is not positive, discontinue use. Store in a cool and dry place

*CLAIMS BASED ON TRADITIONAL HOMEOPATHIC PRACTICE, NOT ACCEPTED MEDICAL EVIDENCE NOT FDA EVALUATED.
This product is not intended to diagnose, treat, cure, or prevent any disease.

Warnings and Storage:

Ask a professional before use if pregnant or breastfeeding or if you have severe symptoms.

Keep away from children. If you have a reaction to this product that is not positive, discontinue use. Store in a cool and dry place

*CLAIMS BASED ON TRADITIONAL HOMEOPATHIC PRACTICE, NOT ACCEPTED MEDICAL EVIDENCE NOT FDA EVALUATED.
This product is not intended to diagnose, treat, cure, or prevent any disease.

Uses
Temporarily relieves occasional discomfort and stiffness that improve with movement, aches aggravated by cold, damp and stormy weather, and feelings of joint weakness.*

Uses
Temporarily relieves occasional discomfort and stiffness that improve with movement, aches aggravated by cold, damp and stormy weather, and feelings of joint weakness.*

Entire package label